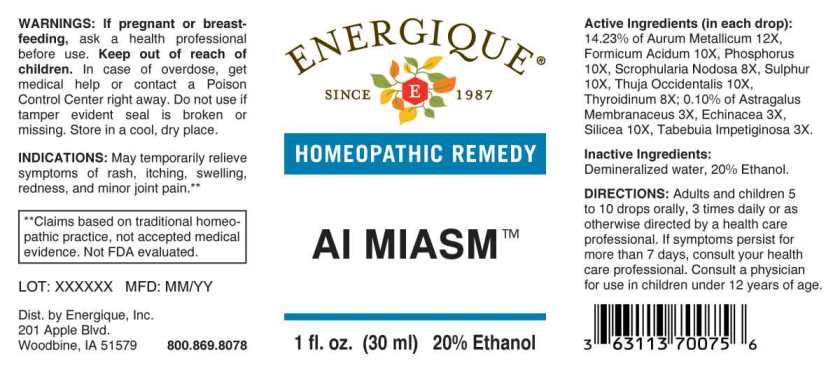 DRUG LABEL: AI Miasm
NDC: 44911-0628 | Form: LIQUID
Manufacturer: Energique, Inc.
Category: homeopathic | Type: HUMAN OTC DRUG LABEL
Date: 20240502

ACTIVE INGREDIENTS: ASTRAGALUS PROPINQUUS ROOT 3 [hp_X]/1 mL; ECHINACEA ANGUSTIFOLIA WHOLE 3 [hp_X]/1 mL; HANDROANTHUS IMPETIGINOSUS BARK 3 [hp_X]/1 mL; SCROPHULARIA NODOSA WHOLE 8 [hp_X]/1 mL; THYROID 8 [hp_X]/1 mL; FORMIC ACID 10 [hp_X]/1 mL; PHOSPHORUS 10 [hp_X]/1 mL; SILICON DIOXIDE 10 [hp_X]/1 mL; SULFUR 10 [hp_X]/1 mL; THUJA OCCIDENTALIS LEAFY TWIG 10 [hp_X]/1 mL; GOLD 12 [hp_X]/1 mL
INACTIVE INGREDIENTS: WATER; ALCOHOL

DRUG FACTS:

ACTIVE INGREDIENTS:

(in each drop): 14.23% of Aurum Metallicum 12X, Formicum Acidum 10X, Phosphorus 10X, Scrophularia Nodosa 8X, Sulphur 10X, Thuja Occidentalis 10X, Thyroidinum (Suis) 8X; 0.10% of Astragalus Membranaceus 3X, Echinacea (Angustifolia) 3X, Silicea 10X, Tabebuia Impetiginosa 3X.

INDICATIONS:

May temporarily relieve symptoms of rash, itching, swelling, redness, and minor joint pain.**

**Claims based on traditional homeopathic practice, not accepted medical evidence. Not FDA evaluated.

WARNINGS:

If pregnant or breast-feeding, ask a health professional before use.

Keep out of reach of children. In case of overdose, get medical help or contact a Poison Control Center right away.

Do not use if tamper evident seal is broken or missing. Store in a cool, dry place.

KEEP OUT OF REACH OF CHILDREN:

In case of overdose, get medical help or contact a Poison Control Center right away.

DIRECTIONS:

Adults and children 5 to 10 drops orally, 3 times daily or as otherwise directed by a health care professional. If symptoms persist for more than 7 days, consult your health care professional. Consult a physician for use in children under 12 years of age.

INDICATIONS:

May temporarily relieve symptoms of rash, itching, swelling, redness, and minor joint pain.**

**Claims based on traditional homeopathic practice, not accepted medical evidence. Not FDA evaluated.

INACTIVE INGREDIENTS:

Demineralized water, 20% Ethanol.

QUESTIONS:

Dist. by Energique, Inc.

201 Apple Blvd.

Woodbine, IA 51579 800-869-8078

PACKAGE LABEL DISPLAY:

ENERGIQUE
SINCE 1987
HOMEOPATHIC REMEDY
AI MIASM
1 fl. oz. (30 ml)